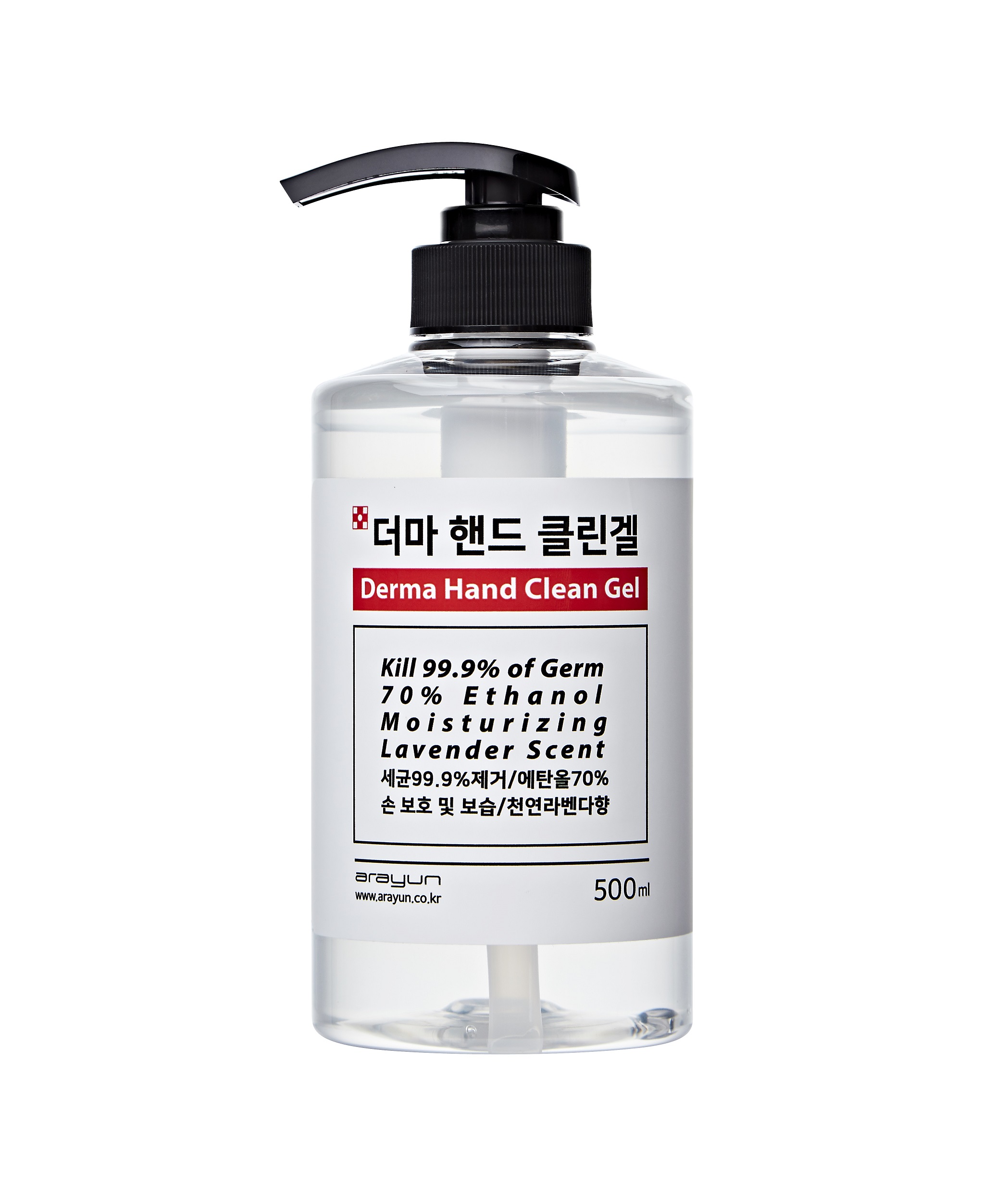 DRUG LABEL: ARAYUN Derma Hand Clean gel
NDC: 76673-0001 | Form: GEL
Manufacturer: RNS Inc
Category: otc | Type: HUMAN OTC DRUG LABEL
Date: 20200430

ACTIVE INGREDIENTS: ALCOHOL 66.5 mL/100 mL
INACTIVE INGREDIENTS: BUTYLENE GLYCOL; GLYCERIN; LAVENDER OIL; CARBOMER 940; WATER

Drug Facts

ACTIVE INGREDIENT

alcohol

INACTIVE INGREDIENT

Water
Propylene Glycol
Glycerin
Cabomer
Triethanolamine
Butylene Glycol
Lavandula Angustifolia (Lavender) Oil
Disodium EDTA
Centella Asiatica Extract
Propolis Extract
Anemarrhena Asphodeloides Root
Arctium Lappa Seed Extract
Nelumbo Nucifera Seed Extract
Forsythia Suspensa Fruit Extract
Platycodon Grandiflorus Root Extract
Lonicera Japonica (Honeysuckle) Flower Extract

PURPOSE

Sterilization of hands and skin

KEEP OUT OF REACH OF THE CHILDREN

INDICATIONS AND USAGE

Apply to clean, dry hands. Apply sufficient amount to thoroughly wet all surfaces of hands and fingers. Rub onto hands until dry.

Supervise children in the use of this product.

WARNINGS

■ Flammable. Keep away from fire or flame.

■ For external use only.

■ Do not use in eyes.

■ lf swallowed, get medical help promptly.

■ Stop use, ask doctor lf irritation occurs.

■ Keep out of reach of children.

DOSAGE AND ADMINISTRATION

for external use only